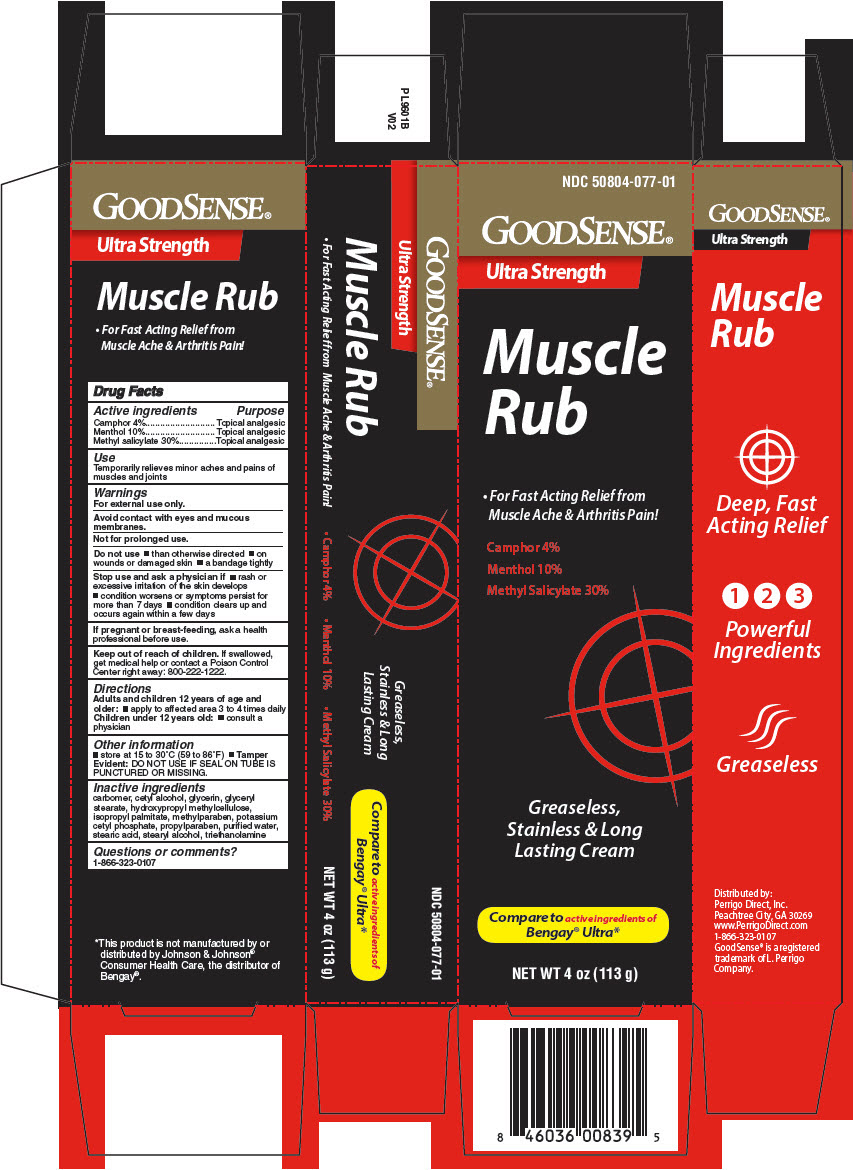 DRUG LABEL: GOOD SENSE ULTRA STRENGTH MUSCLE RUB
NDC: 50804-077 | Form: CREAM
Manufacturer: GOOD SENSE
Category: otc | Type: HUMAN OTC DRUG LABEL
Date: 20241231

ACTIVE INGREDIENTS: CAMPHOR, (-)- 40 mg/1 g; MENTHOL, UNSPECIFIED FORM 100 mg/1 g; METHYL SALICYLATE 300 mg/1 g
INACTIVE INGREDIENTS: CARBOMER HOMOPOLYMER, UNSPECIFIED TYPE; CETYL ALCOHOL; GLYCERIN; GLYCERYL MONOSTEARATE; ISOPROPYL PALMITATE; METHYLPARABEN; POTASSIUM CETYL PHOSPHATE; PROPYLPARABEN; WATER; STEARIC ACID; STEARYL ALCOHOL; TROLAMINE

GOOD SENSE® ULTRA STRENGTH MUSCLE RUB
TOPICAL

Drug Facts

ACTIVE INGREDIENT

Active ingredients | Purpose
Camphor 4% | Topical analgesic
Menthol 10% | Topical analgesic
Methyl salicylate 30% | Topical analgesic

Use

Temporarily relieves minor aches and pains of muscles and joints

Warnings

For external use only.

Avoid contact with eyes and mucus membranes.

Not for prolonged use.

Do not use

- than otherwise directed
- on wounds or damaged skin
- a bandage tightly

Stop use and ask a physician if

- rash or excessive irritation of the skin develops
- condition worsens or symptoms persist for more than 7 days
- condition clears up and occurs again within a few days

PREGNANCY OR BREAST FEEDING

If pregnant or breast-feeding, ask a health professional before use.

Keep out of reach of children. If swallowed, get medical help or contact a Poison Control Center right away: 800-222-1222.

Directions

Adults and children 12 years of age and older:

- apply to affected area 3 to 4 times daily

Children under 12 years old:

- consult a physician

Other information

- store at 15 to 30°C (59 to 86°F)
- Tamper Evident: DO NOT USE IF SEAL ON TUBE IS PUNCTURED OR MISSING.

Inactive ingredients

carbomer, cetyl alcohol, glycerin, glyceryl stearate, isopropyl palmitate, methylparaben, potassium cetyl phosphate, propylparaben, purified water, stearic acid, stearyl alcohol, triethanolamine

Questions or comments?

1-866-323-0107

Distributed by:
Geiss, Destin & Dunn, Inc.
Peachtree City, GA 30269

PRINCIPAL DISPLAY PANEL - 113 g Tube Carton

NDC 50804-077-01

GOODSENSE®

Ultra Strength

Muscle
Rub

- For Fast Acting Relief from
  Muscle Ache & Arthritis Pain!

Camphor 4%
Menthol 10%
Methyl Salicylate 30%

Greaseless,
Stainless & Long
Lasting Cream

Compare to active ingredients of
Bengay® Ultra*

NET WT 4 oz (113 g)